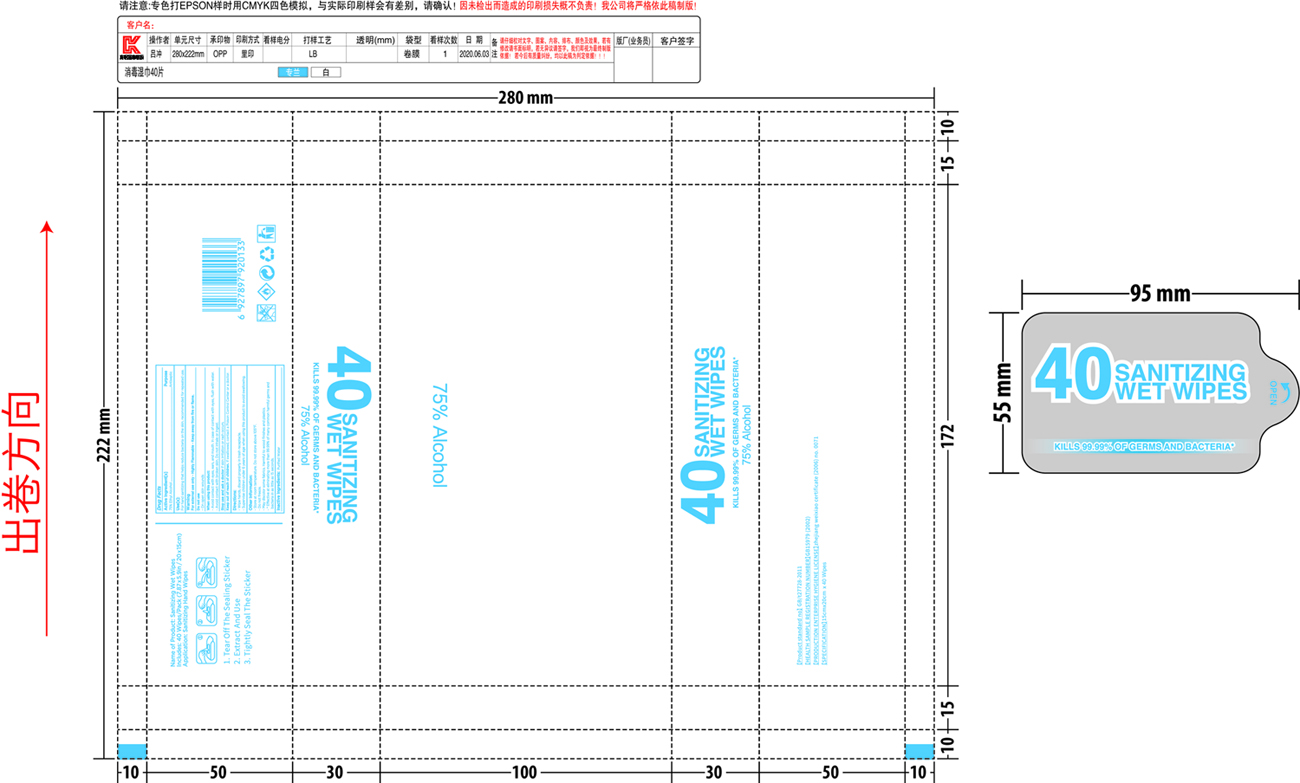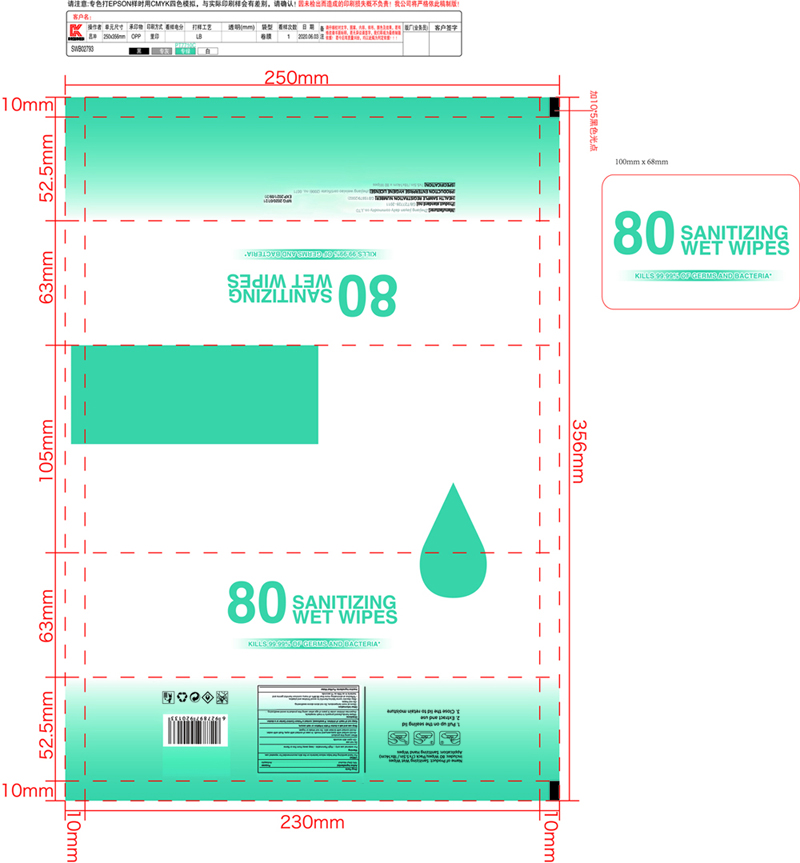 DRUG LABEL: sanitizing wipes
NDC: 42003-013 | Form: CLOTH
Manufacturer: Zhejiang jiayan daily commodity Co.,ltd
Category: otc | Type: HUMAN OTC DRUG LABEL
Date: 20200827

ACTIVE INGREDIENTS: ALCOHOL 0.75 mL/1 g
INACTIVE INGREDIENTS: WATER

sanitizing wipes

Active Ingredient[s]

75% Ethyl Alcohol. Purpose: Antiseptic

Purpose

Antiseptic

Use[s]

For hand saniizing that helps reduce bacteria on the skin, recommened for repeated use

Warning

For external use only - Highly Flammable - Keep away from fire or flame.

Do not use

- On open skin wounds

When using this product

- Avoid contact with eyes, ears, and mouth. In case of contact with eyes, flush with water.

- Avoid contact with broken skin. Do not inhale or ingest.

Stop use and ask a doctor

if skin irritation or rash occurs

Keep out of reach of children.

If swallowed, contact a Poison Control Center or a doctor.

Directions

- Wipe hands, discard properly in trash receptacle.

- Supervise children under 6 years of age when using this product to avoid swallowing

Other information

- Store at room temperaure. Do not store above 105F

- Do not freeze.

- May discolor some fabrics. Harmful to wood finishes and plastics.

- *Effective at eliminating more than 99.99% of many common harmful germs and bacteria in as little as 15 seconds.

Inactive ingredients

Purified water

Package Label - Principal Display Panel

40 PCS NDC: 42003-013-01

40 SANITIZING

WET WIPES

KILLS 99.99% OF GERMS AND BACTERIA*

75% Alcohol

80 PCS NDC: 42003-013-02

80 SANITIZING

WET WIPES

KILLS 99.99% OF GERMS AND BACTERIA*